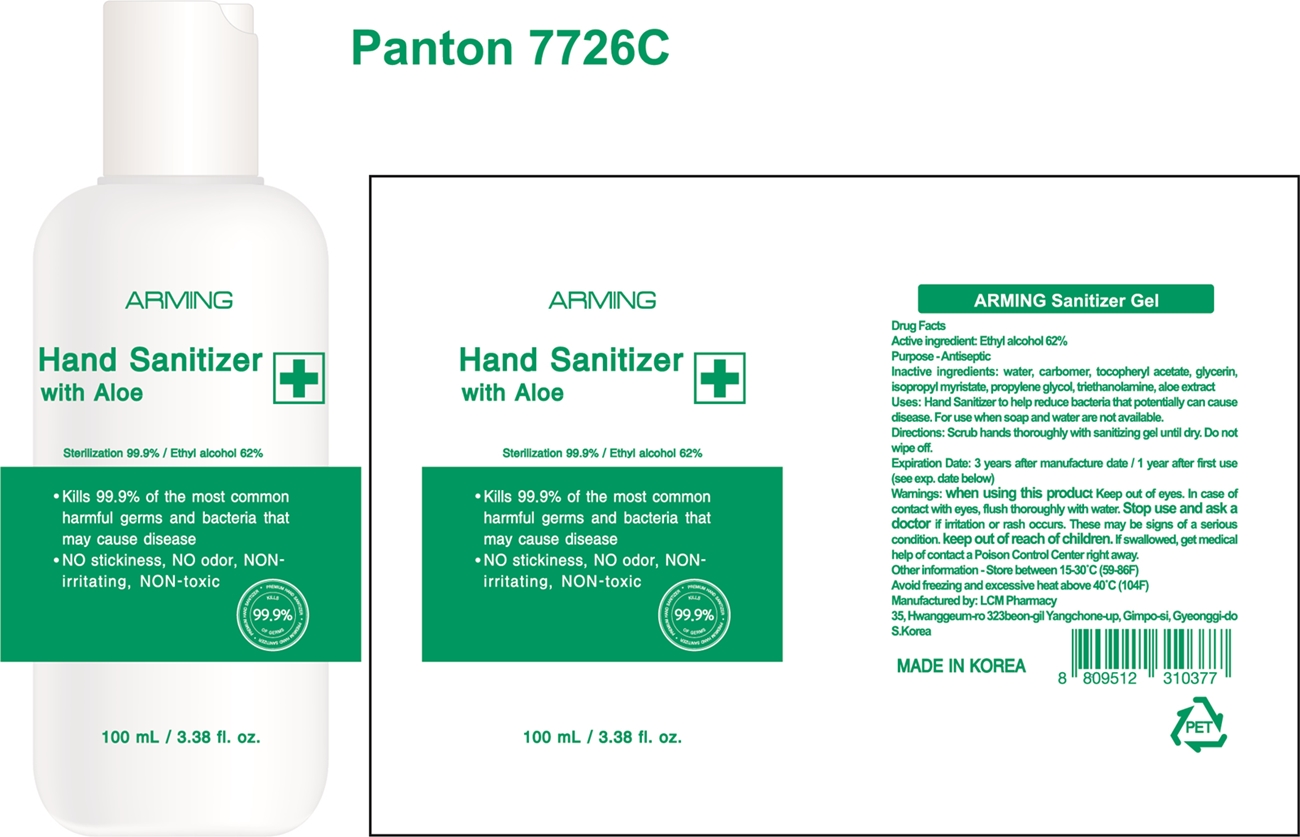 DRUG LABEL: ARMING Sanitizer Gel
NDC: 78250-201 | Form: GEL
Manufacturer: LCM PHAMACY
Category: otc | Type: HUMAN OTC DRUG LABEL
Date: 20200523

ACTIVE INGREDIENTS: ALCOHOL 62 mL/100 mL
INACTIVE INGREDIENTS: TROLAMINE; ISOPROPYL MYRISTATE; PROPYLENE GLYCOL; WATER; GLYCERIN; CARBOMER HOMOPOLYMER, UNSPECIFIED TYPE; ALPHA-TOCOPHEROL ACETATE; ALOE

Active ingredient

Ethyl alcohol 62%

Purpose

Antiseptic

Inactive ingredients

water, carbomer, tocopheryl acetate, glycerin, isopropyl myristate, propylene glycol, triethanolamine, aloe extract

Uses

Hand Sanitizer to help reduce bacteria that potentially can cause disease. For use when soap and water are not available.

Directions

Scrub hands thoroughly with sanitizing gel until dry. Do not wipe off.

when using this product

Keep out of eyes. In case of contact with eyes, flush thoroughly with water.

Stop use and ask a doctor

if irritation or rash occurs. These may be signs of a serious condition.

keep out of reach of children.

If swallowed, get medical help of contact a Poison Control Center right away.

Other information

Store between 15-30C (59-86F)

Avoid freezing and excessive heat above 40C (104F)